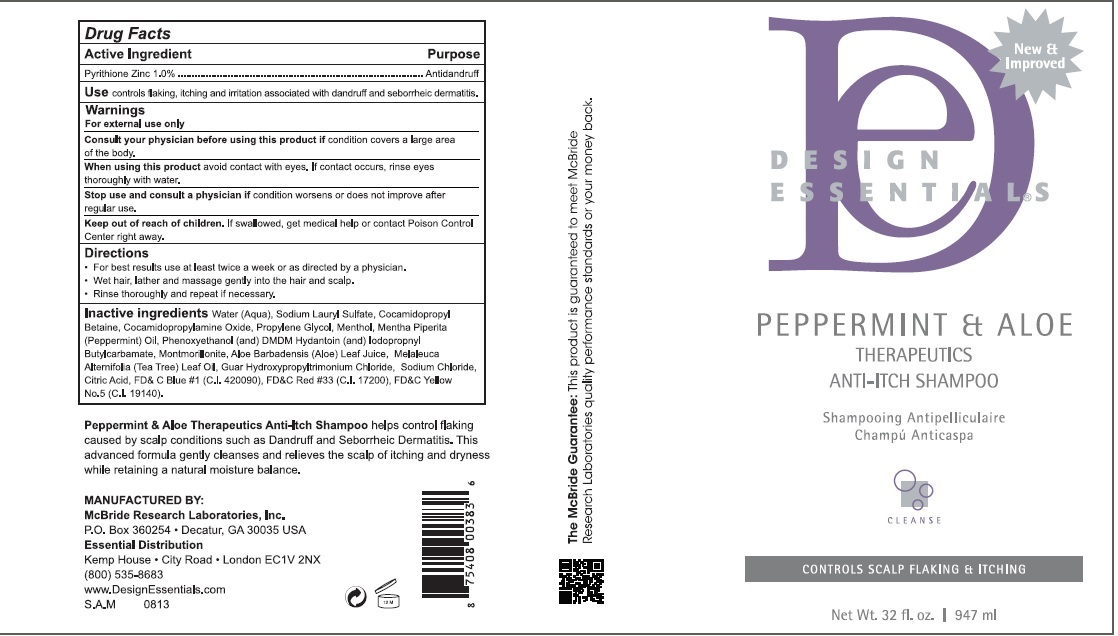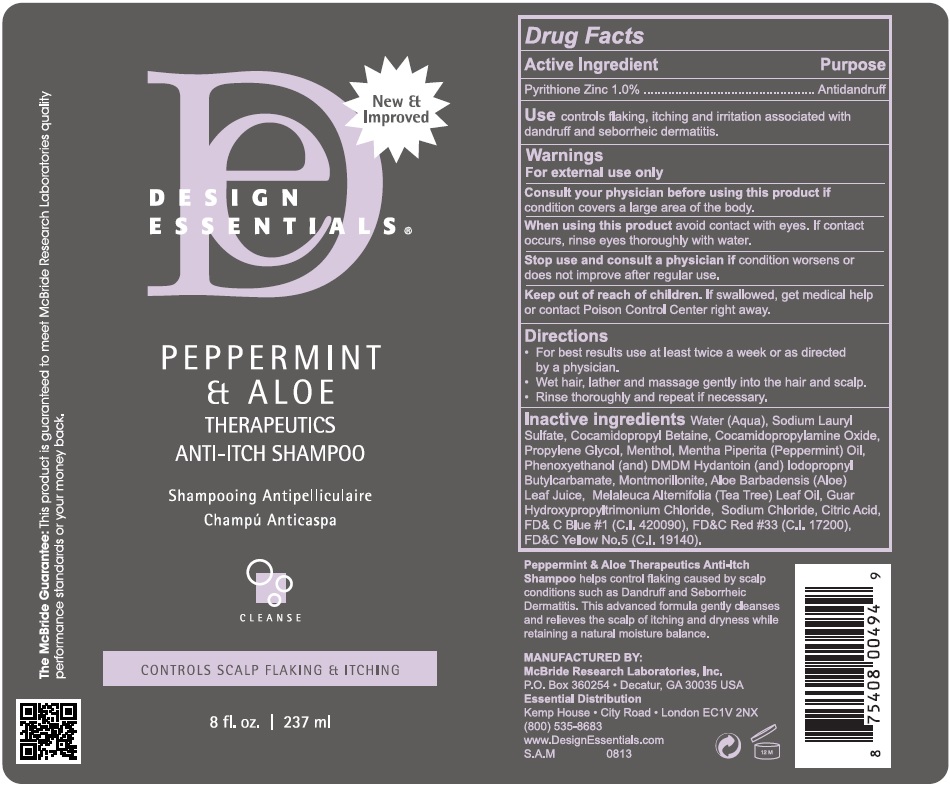 DRUG LABEL: DESIGN ESSENTIALS PEPPERMINT - ALOE THERAPEUTICS
NDC: 69527-122 | Form: SHAMPOO
Manufacturer: .McBride Research Laboratories, Inc.
Category: otc | Type: HUMAN OTC DRUG LABEL
Date: 20160120

ACTIVE INGREDIENTS: PYRITHIONE ZINC 10 mg/1 mL
INACTIVE INGREDIENTS: WATER; SODIUM LAURYL SULFATE; COCAMIDOPROPYL BETAINE; COCAMIDOPROPYLAMINE OXIDE; PROPYLENE GLYCOL; MENTHOL; PEPPERMINT OIL; PHENOXYETHANOL; DMDM HYDANTOIN; IODOPROPYNYL BUTYLCARBAMATE; MONTMORILLONITE; ALOE VERA LEAF; TEA TREE OIL; GUAR HYDROXYPROPYLTRIMONIUM CHLORIDE (1.7 SUBSTITUENTS PER SACCHARIDE); SODIUM CHLORIDE; CITRIC ACID MONOHYDRATE; FD&C BLUE NO. 1; D&C RED NO. 33; FD&C YELLOW NO. 5

DESIGN ESSENTIALS PEPPERMINT & ALOE THERAPEUTICS ANTI-ITCH SHAMPOO

Active Ingredients:

Pyrithione Zinc 1%

Purpose: Antidandruff

INDICATIONS AND USAGE

Use: controls flaking, itching and irritation associated with dandruff and seborrheic dermatitis

Warnings:

- For external use only.

When using this product Avoid contact with eyes. If contact occurs, rinse eyes thoroughly with water.

ASK DOCTOR

Consult your physician before using this product if condition covers a large area of the body.

Stop use and consult a physician if condition worsens or does not improve after regular use.

Keep out of reach of children. If swallowed, get medical help or contact Poison Control Center right away.

Directions

• For best results use at least twice a week or as directed by a physician.

• Wet hair, lather and massage gently into the hair and scalp.

• Rinse thoroughly and repeat if necessary.

Inactive Ingredients

Water (Aqua), Sodium Lauryl Sulfate, Cocamidopropyl Betaine, Cocamidopropylamine Oxide, Propylene Glycol, Menthol, Mentha Piperita(Peppermint) Oil, Phenoxyethanol (and) DMDM Hydantoin (and) Iodopropnyl Butylcarbamate, Montmorillonite, Aloe Barbadensis (Aloe) Leaf Juice, Melaleuca Alternifolia (Tea Tree) Leaf Oil, Guar Hydroxypropyltrimonium Chloride, Sodium Chloride, Citric Acid, FD& C Blue #1 (C.I. 420090), FD&C Red #33 (C.I. 17200), FD&C Yellow No.5 (C.I. 19140).